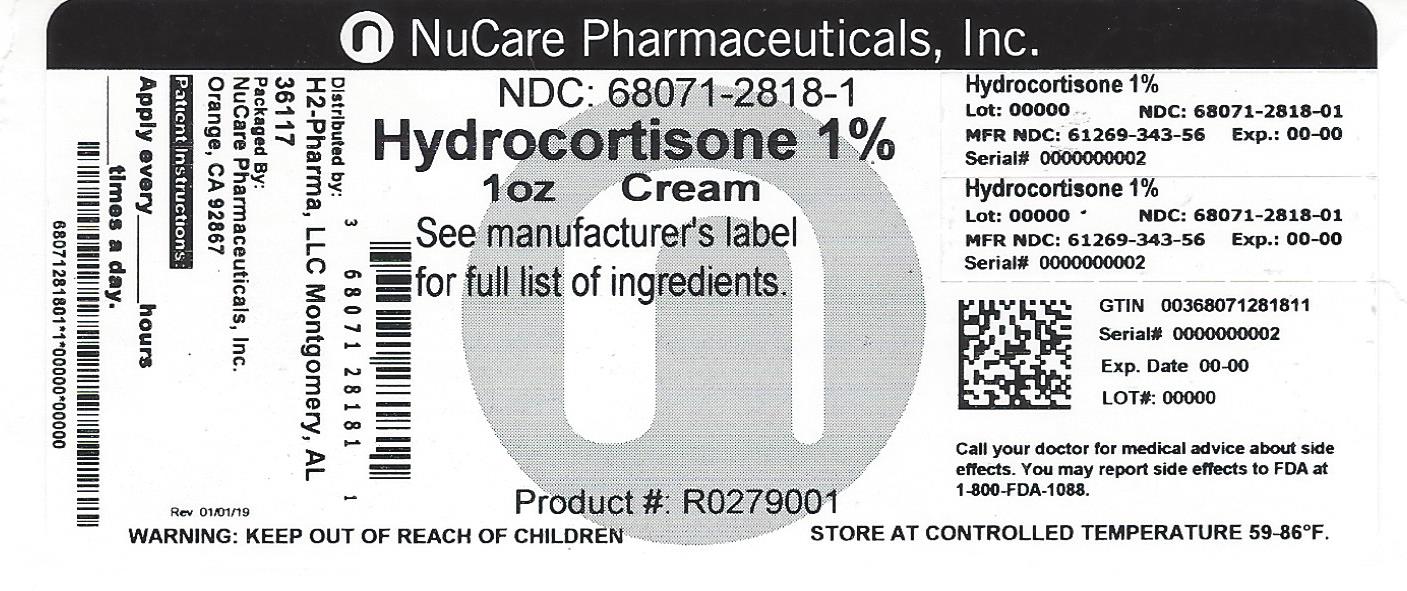 DRUG LABEL: HYDROCORTISONE
NDC: 68071-2818 | Form: CREAM
Manufacturer: NuCare Pharmaceuticals,Inc.
Category: otc | Type: HUMAN OTC DRUG LABEL
Date: 20220823

ACTIVE INGREDIENTS: HYDROCORTISONE 1 g/100 g
INACTIVE INGREDIENTS: CETYL ALCOHOL; GLYCERYL MONOSTEARATE; ISOPROPYL MYRISTATE; METHYLPARABEN; POLYOXYL 40 STEARATE; POLYSORBATE 60; PROPYLENE GLYCOL; PROPYLPARABEN; WATER; SORBIC ACID; SORBITAN MONOSTEARATE; STEARYL ALCOHOL; WHITE WAX

Hydrocortisone Maximum Strength

Drug Facts

Active ingredient

Hydrocortisone, USP 1%

Purpose

Anti-itch

Uses

- temporarily relieves itching associated with minor skin irritations, inflammation, and rashes due to
  - eczema
  - psoriasis
  - insect bites
  - poison ivy, oak, sumac
  - detergents
  - jewelry
  - cosmetics
  - soaps
  - seborrheic dermatitis
- temporarily relieves external anal and genital itching
- other uses of this product should be only under the advice and supervision of a doctor

Warnings

For external use only.

Do not use

- in the genital area if you have a vaginal discharge. Consult a doctor.
- for the treatment of diaper rash. Consult a doctor.

When using this product

- avoid contact with the eyes
- do not use more than directed unless directed by a doctor
- do not put directly into the rectum by using fingers or any mechanical device or applicator

Stop use and ask a doctor if

- condition worsens, symptoms persist for more than 7 days or clear up and occur again within a few days
- do not begin the use of any other hydrocortisone product unless directed by a doctor
- rectal bleeding occurs

Keep out of reach of children. If swallowed, get medical help or contact a Poison Control Center (1-800-222-1222) right away.

Directions

- for itching of skin irritation, inflammation, and rashes
  - adults and children 2 years of age and older: apply to affected area not more than 3 to 4 times daily
  - children under 2 years of age: consult a doctor
- for external anal and genital itching
  - adults: when practical, clean the affected area with mild soap and warm water; rinse thoroughly
  - gently dry by patting or blotting with toilet tissue or a soft cloth before application of this product
  - apply to affected area not more than 3 to 4 times daily
  - children under 12 years of age: consult a doctor

Other information

- store at 15°-30°C (59°-86°F). Protect from freezing.
- before using any medication, read all label directions. Keep carton, it contains important information.

Inactive ingredients

cetyl alcohol, citric acid [Contains one or more of these ingredients to adjust pH] , glyceryl stearate, isopropyl myristate, methylparaben, polyoxyl 40 stearate, polysorbate 60, propylene glycol, propylparaben, purified water, sodium citrate solution , sorbic acid, sorbitan monostearate, stearyl alcohol, white wax

Questions or comments?

Call 1-877-753-3935 Monday-Friday 9AM-5PM EST

Distributed by: H2-Pharma, LLC
Montgomery, AL 36117